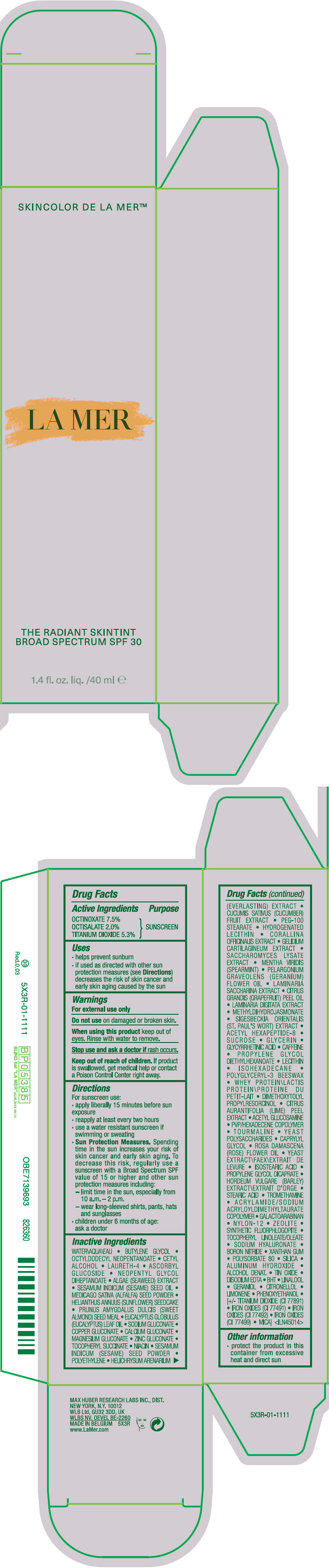 DRUG LABEL: LA MER THE RADIANT SKINTINT BROAD SPECTRUM SPF 30
NDC: 65966-021 | Form: CREAM
Manufacturer: MAX HUBER RESEARCH LAB INC
Category: otc | Type: HUMAN OTC DRUG LABEL
Date: 20231030

ACTIVE INGREDIENTS: OCTINOXATE 75 mg/1 mL; OCTISALATE 20 mg/1 mL; TITANIUM DIOXIDE 53 mg/1 mL
INACTIVE INGREDIENTS: EUCALYPTUS GUM; SODIUM GLUCONATE; COPPER GLUCONATE; CALCIUM GLUCONATE; MAGNESIUM GLUCONATE; ZINC GLUCONATE; .ALPHA.-TOCOPHEROL SUCCINATE, D-; WATER; NIACIN; SESAME SEED; HIGH DENSITY POLYETHYLENE; GAMOCHAETA PURPUREA FLOWER; CUCUMBER; PEG-100 STEARATE; HYDROGENATED SOYBEAN LECITHIN; CORALLINA OFFICINALIS; PLOCAMIUM CARTILAGINEUM; SACCHAROMYCES LYSATE; SPEARMINT; PELARGONIUM GRAVEOLENS FLOWER OIL; SACCHARINA LATISSIMA; CITRUS MAXIMA FRUIT RIND OIL; LAMINARIA DIGITATA; METHYL DIHYDROJASMONATE (SYNTHETIC); ACETYL HEXAPEPTIDE-8; SUCROSE; GLYCERIN; ENOXOLONE; CAFFEINE; PROPYLENE GLYCOL DIETHYLHEXANOATE; ISOHEXADECANE; DIMETHOXYTOLYL PROPYLRESORCINOL; LIME PEEL; N-ACETYLGLUCOSAMINE; CAPRYLYL GLYCOL; ROSA X DAMASCENA FLOWER OIL; YEAST, UNSPECIFIED; ISOSTEARIC ACID; PROPYLENE GLYCOL DICAPRATE; BARLEY; STEARIC ACID; TROMETHAMINE; GALACTOARABINAN; NYLON-12; HYALURONATE SODIUM; BORON NITRIDE; XANTHAN GUM; POLYSORBATE 80; SILICON DIOXIDE; ALUMINUM HYDROXIDE; ALCOHOL; STANNIC OXIDE; EDETATE DISODIUM ANHYDROUS; BUTYLATED HYDROXYTOLUENE; LINALOOL, (+/-)-; GERANIOL; FERRIC OXIDE RED; .BETA.-CITRONELLOL, (R)-; LIMONENE, (+)-; PHENOXYETHANOL; FERRIC OXIDE YELLOW; FERROSOFERRIC OXIDE; MICA; BUTYLENE GLYCOL; OCTYLDODECYL NEOPENTANOATE; CETYL ALCOHOL; LAURETH-4; ASCORBYL GLUCOSIDE; NEOPENTYL GLYCOL DIHEPTANOATE; NORI; SESAME OIL; ALFALFA SEED; HELIANTHUS ANNUUS SEEDCAKE

LA MER THE RADIANT SKINTINT BROAD SPECTRUM SPF 30

Drug Facts

Active Ingredients

OCTINOXATE 7.5%
OCTISALATE 2.0%
TITANIUM DIOXIDE 5.3%

Purpose

SUNSCREEN

Uses

- helps prevent sunburn
- if used as directed with other sun protection measures (see Directions) decreases the risk of skin cancer and early skin aging caused by the sun

Warnings

For external use only

Do not use on damaged or broken skin.

When using this product keep out of eyes. Rinse with water to remove.

Stop use and ask a doctor if rash occurs.

Keep out of reach of children. If product is swallowed, get medical help or contact a Poison Control Center right away.

Directions

For sunscreen use:

- apply liberally 15 minutes before sun exposure
- reapply at least every two hours
- use a water resistant sunscreen if swimming or sweating
- Sun Protection Measures. Spending time in the sun increases your risk of skin cancer and early skin aging. To decrease this risk, regularly use a sunscreen with a Broad Spectrum SPF value of 15 or higher and other sun protection measures including:
  - limit time in the sun, especially from 10 a.m. – 2 p.m.
  - wear long-sleeved shirts, pants, hats and sunglasses
- children under 6 months of age: ask a doctor

Inactive Ingredients

WATER\AQUA\EAU • BUTYLENE GLYCOL • OCTYLDODECYL NEOPENTANOATE • CETYL ALCOHOL • LAURETH-4 • ASCORBYL GLUCOSIDE • NEOPENTYL GLYCOL DIHEPTANOATE • ALGAE (SEAWEED) EXTRACT • SESAMUM INDICUM (SESAME) SEED OIL • MEDICAGO SATIVA (ALFALFA) SEED POWDER • HELIANTHUS ANNUUS (SUNFLOWER) SEEDCAKE • PRUNUS AMYGDALUS DULCIS (SWEET ALMOND) SEED MEAL • EUCALYPTUS GLOBULUS (EUCALYPTUS) LEAF OIL • SODIUM GLUCONATE • COPPER GLUCONATE • CALCIUM GLUCONATE • MAGNESIUM GLUCONATE • ZINC GLUCONATE • TOCOPHERYL SUCCINATE • NIACIN • SESAMUM INDICUM (SESAME) SEED POWDER • POLYETHYLENE • HELICHRYSUM ARENARIUM (EVERLASTING) EXTRACT • CUCUMIS SATIVUS (CUCUMBER) FRUIT EXTRACT • PEG-100 STEARATE • HYDROGENATED LECITHIN • CORALLINA OFFICINALIS EXTRACT • GELIDIUM CARTILAGINEUM EXTRACT • SACCHAROMYCES LYSATE EXTRACT • MENTHA VIRIDIS (SPEARMINT) • PELARGONIUM GRAVEOLENS (GERANIUM) FLOWER OIL • LAMINARIA SACCHARINA EXTRACT • CITRUS GRANDIS (GRAPEFRUIT) PEEL OIL • LAMINARIA DIGITATA EXTRACT • METHYLDIHYDROJASMONATE • SIGESBECKIA ORIENTALIS (ST. PAUL'S WORT) EXTRACT • ACETYL HEXAPEPTIDE-8 • SUCROSE • GLYCERIN • GLYCYRRHETINIC ACID • CAFFEINE • PROPYLENE GLYCOL DIETHYLHEXANOATE • LECITHIN • ISOHEXADECANE • POLYGLYCERYL-3 BEESWAX • WHEY PROTEIN\LACTIS PROTEIN\PROTEINE DU PETIT-LAIT • DIMETHOXYTOLYL PROPYLRESORCINOL • CITRUS AURANTIFOLIA (LIME) PEEL EXTRACT • ACETYL GLUCOSAMINE • PVP/HEXADECENE COPOLYMER • TOURMALINE • YEAST POLYSACCHARIDES • CAPRYLYL GLYCOL • ROSA DAMASCENA (ROSE) FLOWER OIL • YEAST EXTRACT\FAEX\EXTRAIT DE LEVURE • ISOSTEARIC ACID • PROPYLENE GLYCOL DICAPRATE • HORDEUM VULGARE (BARLEY) EXTRACT\EXTRAIT D'ORGE • STEARIC ACID • TROMETHAMINE • ACRYLAMIDE/SODIUM ACRYLOYLDIMETHYLTAURATE COPOLYMER • GALACTOARABINAN • NYLON-12 • ZEOLITE • SYNTHETIC FLUORPHLOGOPITE • TOCOPHERYL LINOLEATE/OLEATE • SODIUM HYALURONATE • BORON NITRIDE • XANTHAN GUM • POLYSORBATE 80 • SILICA • ALUMINUM HYDROXIDE • ALCOHOL DENAT. • TIN OXIDE • DISODIUM EDTA • BHT • LINALOOL • GERANIOL • CITRONELLOL • LIMONENE • PHENOXYETHANOL • [+/- TITANIUM DIOXIDE (CI 77891) • IRON OXIDES (CI 77491) • IRON OXIDES (CI 77492) • IRON OXIDES (CI 77499) • MICA] <ILN45014>

Other information

- protect the product in this container from excessive heat and direct sun

PRINCIPAL DISPLAY PANEL - 40 ml Tube Carton

SKINCOLOR DE LA MER™

LA MER

THE RADIANT SKINTINT
BROAD SPECTRUM SPF 30

1.4 fl. oz. liq. /40 ml e